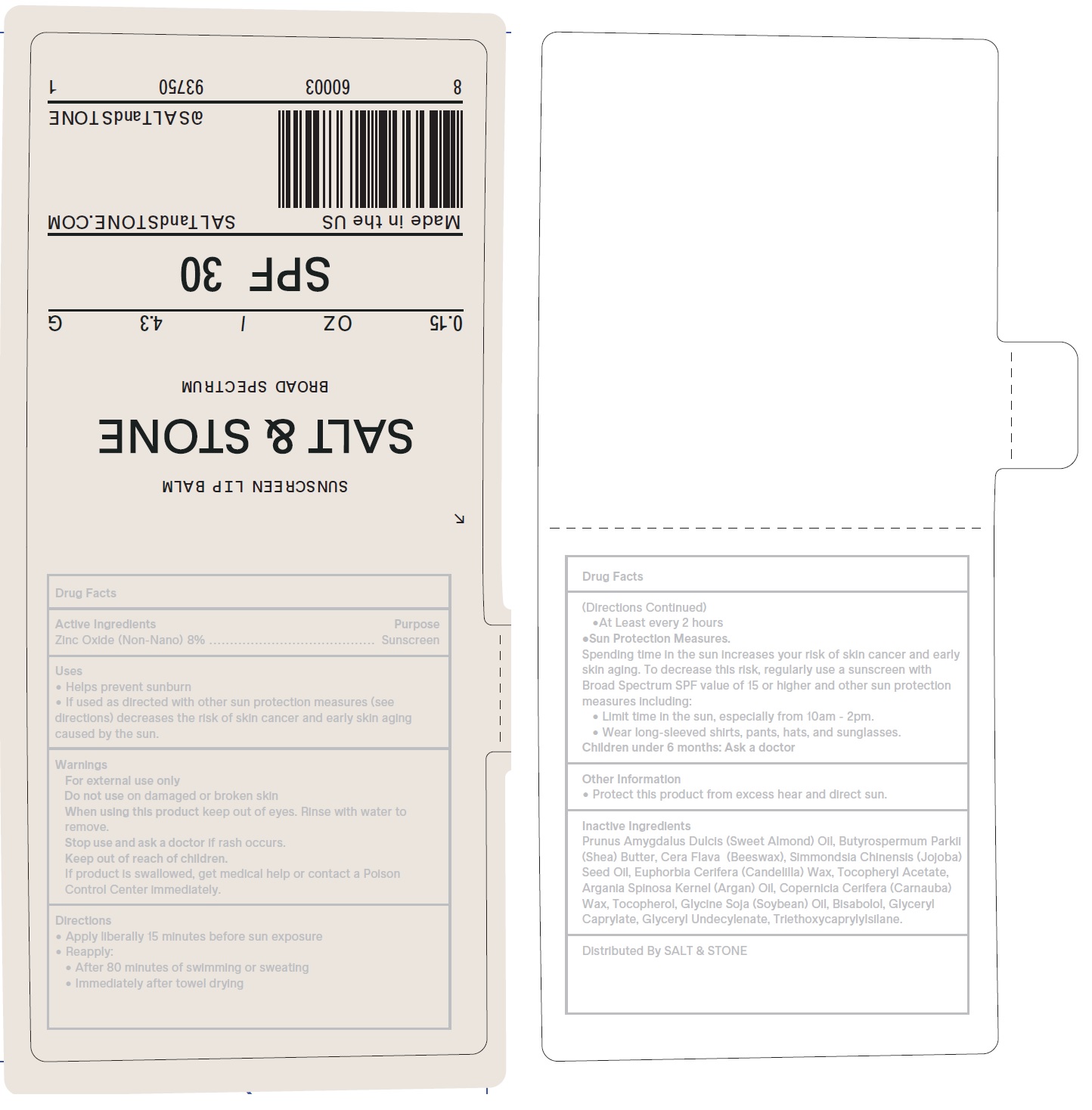 DRUG LABEL: Salt and Stone Sunscreen Lip Balm SPF 30
NDC: 71585-139 | Form: STICK
Manufacturer: Salt and Stone LLC
Category: otc | Type: HUMAN OTC DRUG LABEL
Date: 20250130

ACTIVE INGREDIENTS: ZINC OXIDE 0.08 g/1 g
INACTIVE INGREDIENTS: ALMOND OIL; SHEA BUTTER; CANDELILLA WAX; .ALPHA.-TOCOPHEROL ACETATE; CARNAUBA WAX; TOCOPHEROL; SOYBEAN OIL; LEVOMENOL; GLYCERYL MONOCAPRYLATE; GLYCERYL 1-UNDECYLENATE; TRIETHOXYCAPRYLYLSILANE

Salt & Stone Sunscreen Lip Balm SPF 30, 0.15 Oz.(4.3 g)

Active Ingredients

Zinc Oxide (Non-Nano) 8 %

Purpose

Sunscreen

Uses

• Helps prevent sunburn. • If used as directed with other sun protection measures (see directions), decreases the risk of skin cancer and early skin aging caused by the sun.

Warnings

For external use only.

Do not use on damaged or broken skin

When using this product keep out of eyes. Rinse with water to remove

Stop use and ask a doctor if rash occurs.

Keep out of reach of children.

If product is swallowed, get medical help or contact a Poison Control Center immediately.

Directions

- Apply liberally 15 minutes before sun exposure
- Reapply:
- • After 80 minutes of swimming or sweating • Immediately after towel drying •At Least every 2 hours
- Spending time in the sun increases your risk of skin cancer and early skin aging. To decrease this risk, regularly use a sunscreen with Broad Spectrum SPF value of 15 or higher and other sun protection measures including: • Limit time in the sun, especially from 10am - 2pm. • Wear long-sleeved shirts, pants, hats, and sunglasses. Sun Protection Measures.
- Children under 6 months: Ask a doctor

Other Information

- Protect this product from excess heat and direct sun.

Inactive Ingredients

Prunus Amygdalus Dulcis (Sweet Almond) Oil, Butyrospermum Parkii (Shea) Butter, Cera Flava (Beeswax), Simmondsia Chinensis (Jojoba) Seed Oil, Euphorbia Cerifera (Candelilla) Wax, Tocopheryl Acetate, Argania Spinosa Kernel (Argan) Oil, Copernicia Cerifera (Carnauba) Wax, Tocopherol, Glycine Soja (Soybean) Oil, Bisabolol, GlycerylCaprylate, Glyceryl Undecylenate, Triethoxycaprylylsilane